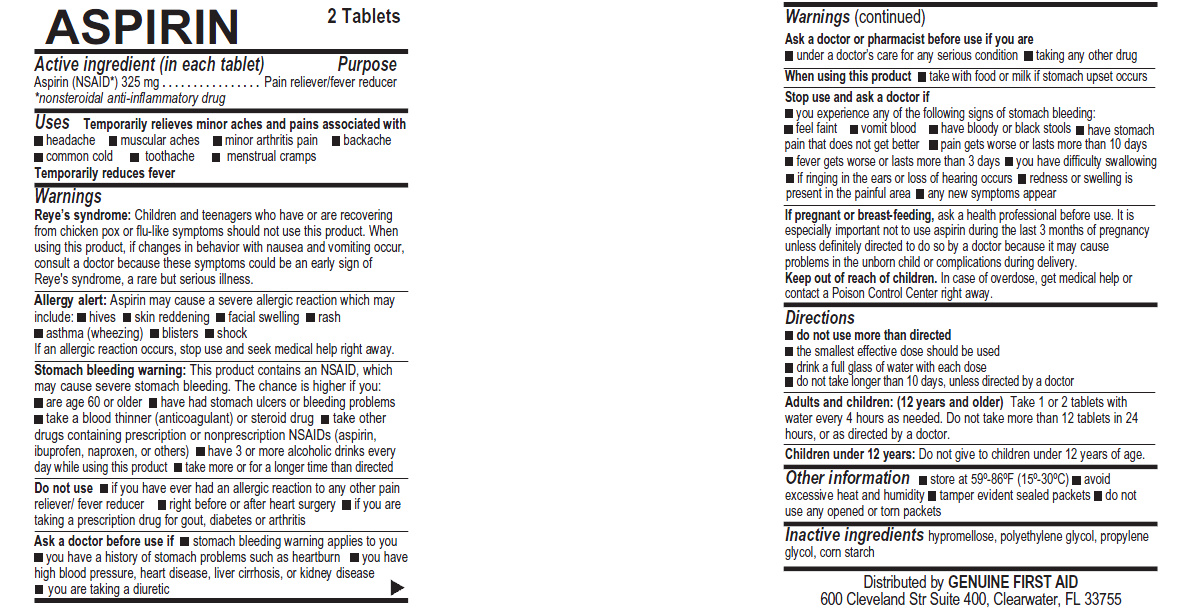 DRUG LABEL: ASPIRIN
NDC: 52124-0011 | Form: TABLET
Manufacturer: Genuine First Aid LLC
Category: otc | Type: HUMAN OTC DRUG LABEL
Date: 20171230

ACTIVE INGREDIENTS: ASPIRIN 325 mg/1 1
INACTIVE INGREDIENTS: HYPROMELLOSES; POLYETHYLENE GLYCOL; PROPYLENE GLYCOL; STARCH, CORN

ASPIRIN 325mg

Active Ingredient (in each tablet)

Aspirin (NSAID*) 325 mg
*nonsteroidal anti-inflammatory drug

Purpose

Pain Reliever / fever reducer

Uses

Temporarily relieves minor aches and pains associated with:
headache ; muscular aches ; minor arthritis pain ; backache ; common cold ; toothache ; menstrual cramps ; Temporarily reduces fever

Warnings

Reye's syndrome: Children and teenagers who have or are recovering from chicken pox of flu-like symptoms should not use this product. When using this product, if changes in behavior with nausea and vomiting occur, consult a doctor because these symptoms could be an early sign of Reye's syndrome, a rare but serious illness.

Allergy alert: Aspirin may cause a severe allergic reaction which may include: hives, skin reddening, facial swelling, rash, asthma (wheezing), blisters, shock, If an allergic reaction occurs, stop use and seek medical help right away.

Stomach bleeding warning: This contains an NSAID, which may cause severe stomach bleeding. The chance is higher if you:
are age 60 or older; have had stomach ulcers or bleeding problems; take a blood thinner (anticoagulant) or steroid drug; take other drugs containing prescription or nonprescription NSAIDs (aspirin, ibuprofen, naproxen, or others); have 3 or more alcoholic drinks every day while using this product; take more or for a longer time than directed

Do not use

if you have ever had an allergic reaction to any other pain reliever/ fever reducer; right before or after heart surgery; if you are taking a prescription drug for gout, diabetes or arthritis

Ask a doctor before use if: stomach bleeding warning applies to you; you have a history of stomach problems such as heartburn; you have high blood pressure, heart disease, liver cirrhosis, or kidney disease; you are taking a diuretic

Ask a doctor or pharmacist before use if you are:

under a doctor's care for any serious condition; taking any other drug

When using this product: take with food or milk if stomach upset occurs

Stop use and ask a doctor if

you experience any of the following signs of stomach bleeding:
feel faint; vomit blood; have bloody or black stools; have stomach
pain that does not get better; pain gets worse or lasts more than 10 days; fever gets worse or lasts more than 3 days; you have difficulty swallowing; if ringing in the ears or loss of hearing occurs; redness or swelling is present in the painful areas; any new symptoms appear

PREGNANCY OR BREAST FEEDING

If pregnant or breast-feeding, ask a health professional before use. It is especially important to use aspirin during the last 3 months of pregnancy unless definitely directed to do so by a doctor because it may cause problems in the unborn child or complications during delivery.

Keep out of reach of children. In case of overdose, get medical help or

contact a Poison Control Center right away.

Directions

do not use more than directed

the smallest effective dose should be used

drink a full glass of water with each dose

do not take longer than 10 days, unless directed by a doctor

DOSAGE AND ADMINISTRATION

Adults and children: (12 years and older) Take 1 or 2 tablets with

water every 4 hours as needed. Do not take more than 12 tablets in 24

hours, or as directed by a doctor.

Children under 12 years: Do not give to children under 12 years of age.

STORAGE AND HANDLING

Store at 59 - 86 degree Fahrenheit (15 - 30 degree Celsius); avoid

excessive heat and humidity; tamper evident sealed packets;

Do not use any opened or torn packets

Inactive Ingredients

hypromellose, polyethylene glycol, propylene glycol, corn starch

DESCRIPTION

Distributed by GENUINE FIRST AID
600 Clevelad Str Suite 400, Clearwater, FL 33755